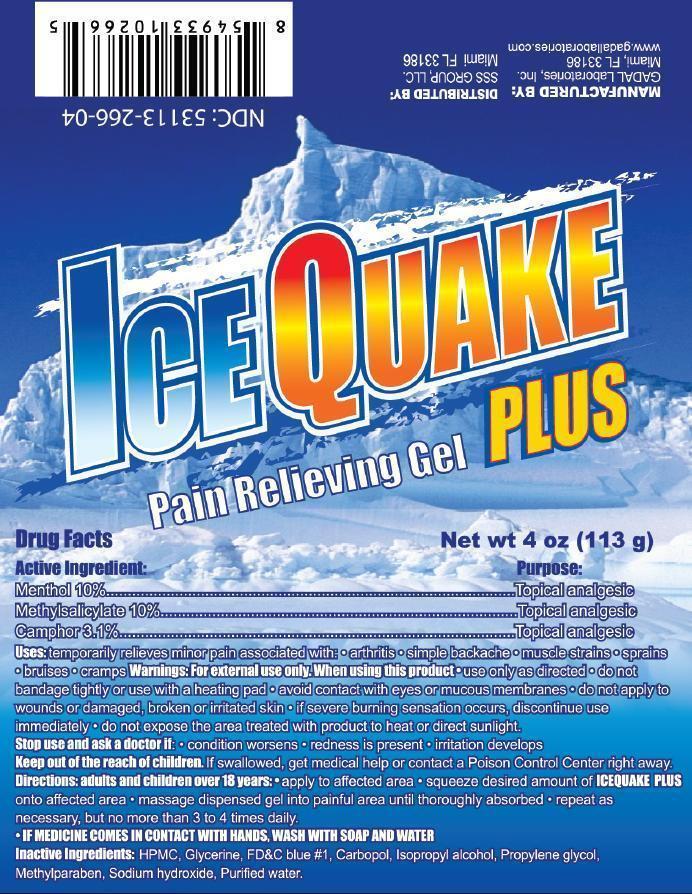 DRUG LABEL: Ice Quake
NDC: 53113-266 | Form: GEL
Manufacturer: Gadal Laboratories Inc
Category: otc | Type: HUMAN OTC DRUG LABEL
Date: 20130927

ACTIVE INGREDIENTS: MENTHOL 10 g/100 g; METHYL SALICYLATE 10 g/100 g; CAMPHOR (SYNTHETIC) 3.1 g/100 g
INACTIVE INGREDIENTS: HYPROMELLOSE 2910 (10000 MPA.S); GLYCERIN; FD&C BLUE NO. 1; CARBOMER HOMOPOLYMER TYPE A (ALLYL PENTAERYTHRITOL CROSSLINKED); ISOPROPYL ALCOHOL; PROPYLENE GLYCOL; METHYLPARABEN; SODIUM HYDROXIDE; WATER

Active Ingredients Purpose

Methyl Salicylate 10% Topical Analgesic

Menthol 10% Topical Analgesic

Camphor 3.1% Topical Analgesic

Purpose

Topical Analgesic

Uses

temporarily relieves minor pain associated with

- arthritis
- simple backache
- muscle strains
- bruises
- sprains
- cramps

Warnings

For external use only

When using this product: Use only as directed

- do not bandage tightly or use with a heating pad
- avoid contact with the eyes and mucous membranes
- do not apply to wounds or damaged, broken or irritated skin
- if sever burning sensation occurs, discontinue use immediately
- do not expose the area treated with product to heat or direct sunlight

Stop use and ask a doctor if

- condition worsens
- redness is present
- irritation develops

Keep out of reach of children. If swallowed get medical help or contact a Poison Control Center right away.

Directions

- adults and children over 12 years:
- apply to affected
- squeeze desired amount of IceQuake Plus onto affected area
- massage dispensed gel into painful area until thoroughly absorbed
- repeat as necessary, but no more than 3 to 4 times daily

INACTIVE INGREDIENT

Inactive ingredients: HPMC, glycerin, FD&C Blue No.1, carbopol, isopropyl alcohol, propylene glycol, methylparaben, sodium hydroxide, water

QUESTIONS

SSS Group, LLC Miami, Fl 33183